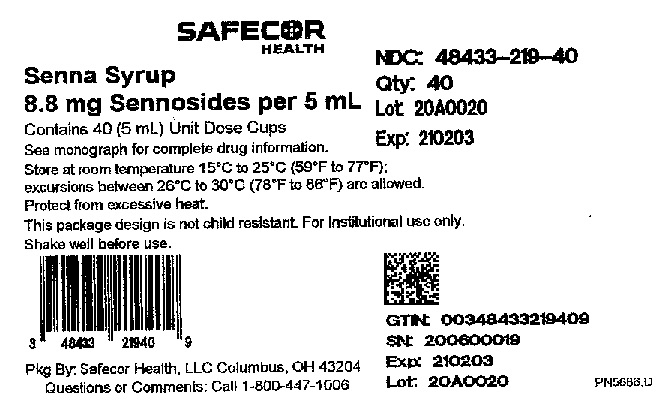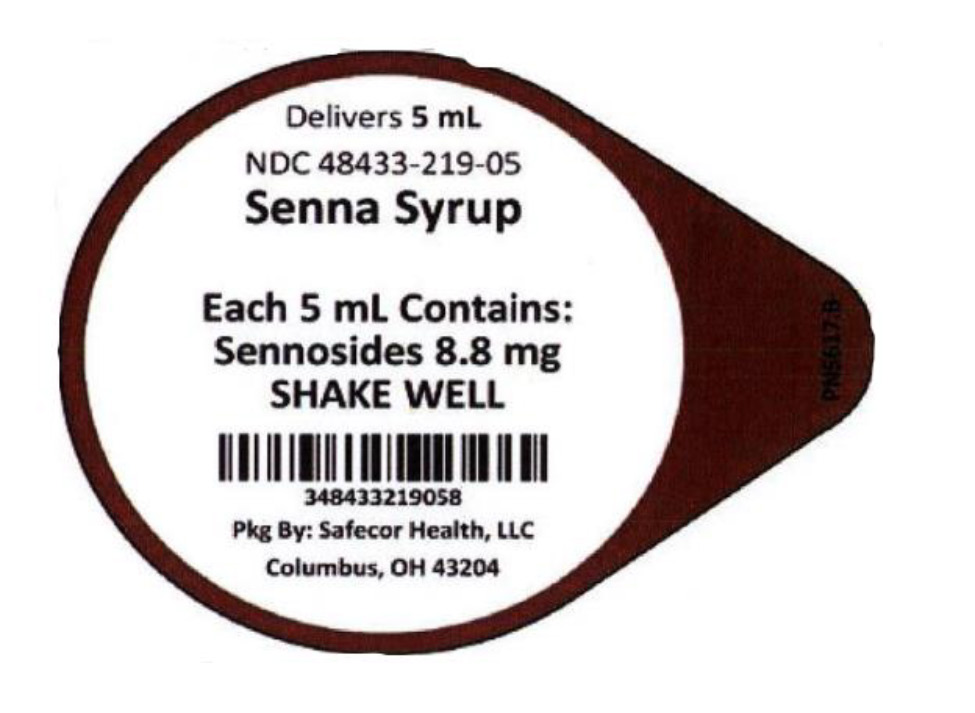 DRUG LABEL: Senna Syrup
NDC: 48433-219 | Form: LIQUID
Manufacturer: Safecor Health, LLC
Category: otc | Type: HUMAN OTC DRUG LABEL
Date: 20250108

ACTIVE INGREDIENTS: SENNOSIDES 8.8 mg/5 mL
INACTIVE INGREDIENTS: METHYLPARABEN; PROPYLENE GLYCOL; PROPYLPARABEN; WATER; SUCROSE

SAFECOR HEALTH
Senna Syrup (8.8 mg/5 mL)
Unit Dose Cup

Drug Facts

Active Ingredient (in each 5 mL = 1 teaspoonful)
Sennosides 8.8 mg

Purpose
Laxative

INDICATIONS AND USAGE

Use: • relieves occasional constipation (irregularity), generally causes bowel movement in 6-12 hours.

WARNINGS

WARNINGS: Do not use • laxative products for a period longer than 1 week unless directed by a doctor

Ask a doctor before use if you have • stomach pain • nausea • vomiting • noticed a sudden change in bowel movement that continues over a period of 2 weeks

Stop use and ask a doctor if you have • rectal bleeding • no bowel movement after use of laxative

These could be signs of a serious condition.

PREGNANCY OR BREAST FEEDING

If pregnant or breast feeding, ask a health care professional before use.

KEEP OUT OF REACH OF CHILDREN

Keep this and all drugs out of reach of children. In case of overdose, get medical help or contact a Poison Control Center immediately. In case of eye contact, flush with water.

Directions:
- Shake well before use
- Do not exceed recommended dose
Age | Starting Dose | Maximum Dosage
Adults and children 12 years of age and over | 2 to 3 teaspoonfuls (10 mL to 15 mL) once a day preferably at bedtime; increase as needed or as recommended by a doctor | 3 teaspoonfuls (15 mL) in the morning and 3 teaspoonfuls (15 mL) at bedtime
Children under 12 years of age | Ask a doctor | Ask a doctor
1 teaspoonful = 5 mL

Other information: Store at room temperature 15°C to 25°C (59°F to 77°F). Excursions between 26°C to 30°C (78°F to 86°F) are allowed. Protect from excessive heat. For more info call 1- 800-447-1006.

INACTIVE INGREDIENT

Inactive ingredients: Artificial and natural chocolate flavor, methylparaben, propylparaben, propylene glycol, sucrose and purified water.

NDC: 48433-219-05 Senna Syrup 8.8 mg/5 mL Unit Dose Cup

Mfd. in the U.S.A.
Distributed by: Safecor Health, LLC
4060 Business Park Drive, Columbus, OH 43204 Rev: 02/2020 PN5497

PACKAGE LABEL

———Principal Display Panel———

SAFECOR HEALTH
NDC: 48433-219-40
Senna Syrup Qty: 40
8.8 mg Sennosides per 5 mL Lot: 20A0020
Contains 40 (5 mL) Unit Dose Cups Exp: 210203
See monograph for complete drug information.
Store at room temperature 15°C to 25°C (59°F to 77°F);
excursions between 26°C to 30°C (78°F to 86°F) are allowed.
Protect from excessive heat.
This package design is not child resistant. For institutional use only.
Shake well before use.
GTIN: 00348433219409
SN: 200600019
Pkg By: Safecor Health, LLC Columbus, OH 43204 Exp: 210203
Questions or Comments: Call 1-800-447-1006 Lot: 20A0020